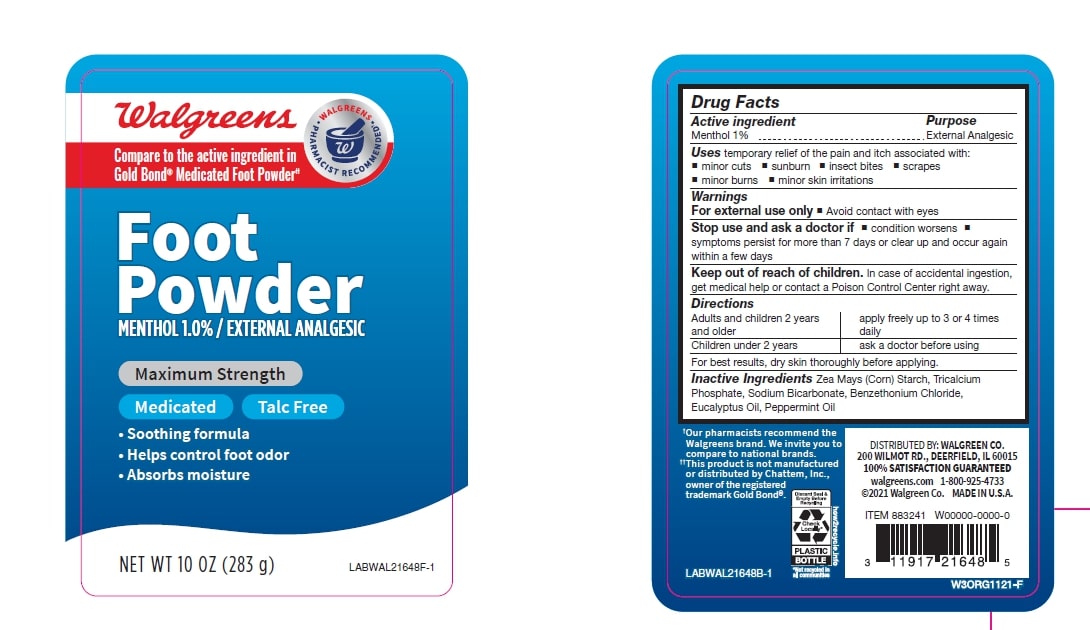 DRUG LABEL: Walgreens Medicated Foot Powder
NDC: 42669-100 | Form: POWDER
Manufacturer: Davion, Inc
Category: otc | Type: HUMAN OTC DRUG LABEL
Date: 20250912

ACTIVE INGREDIENTS: MENTHOL 1 g/100 g
INACTIVE INGREDIENTS: STARCH, CORN; TRICALCIUM PHOSPHATE; SODIUM BICARBONATE; BENZETHONIUM CHLORIDE; EUCALYPTUS OIL; PEPPERMINT OIL

Walgreens Medicated Talc Free Foot Powder

Active Ingredient

Menthol 1.0%

Purpose

External Analgesic

Uses

temporary relief of the pain and itch associated with:

- minor cuts
- sunburn
- insect bites
- scrapes
- minor burns
- minor skin irritations

Warnings

For external use only

When using this product

- Avoid contact with eyes

Stop use and ask a doctor if

- condition worsens
- symptoms persists for more than 7 days or clear up and occur again within a few days

Keep out of reach of children

In case of accidental ingestion, get medical help or contact a Poison Control Center right away.

Directions

- Adults and children 2 years and older - apply freely upto 3 or 4 times daily
- children under 2 years - ask a doctor before using
  For best results, dry skin thoroughly before applying.

Inactive ingredients

Zea Mays (Corn) Starch, Tricalcium Phosphate, Sodium Bicarbonate, Benzethonium Chloride, Eucalyptus Oil, Peppermint Oil